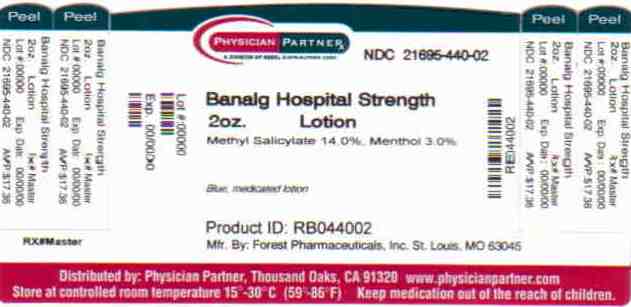 DRUG LABEL: Banalg
NDC: 21695-440 | Form: LOTION
Manufacturer: Rebel Distributors Corp
Category: otc | Type: HUMAN OTC DRUG LABEL
Date: 20110215

ACTIVE INGREDIENTS: METHYL SALICYLATE 140 mg/1 g; MENTHOL 30 mg/1 g
INACTIVE INGREDIENTS: 1,3-DIMETHYLBUTYL SALICYLATE; WATER

Banalg Drug Facts

Active ingredient

Methyl Salicylate 14.0%

Menthol 3.0%

Uses

For the temporary relief of minor ach3es and pains of muscles and joints associated with arthritis and rheumatism. Also good for simple backache, strains and sprains.

Warnings

Use only as directed. If pain persists more than 10 days, or redness is present, or in conditions affecting children under 12 years of age, consult your physician immediately. Discontinue use if excessive irritation of the skin develops. Avoid getting into the eyes or on mucous membranes.

For external use only. Use only as directed. Do not apply to wounds, broken or irritated skin. Do not use with a heating pad. Do not bandage tightly.

If swallowed, induce vomiting and contact a physician or poison control center immediately.

Directions

Apply fast vanishing lotion with gentle massage to affected area not more than 3 to 4 times daily.